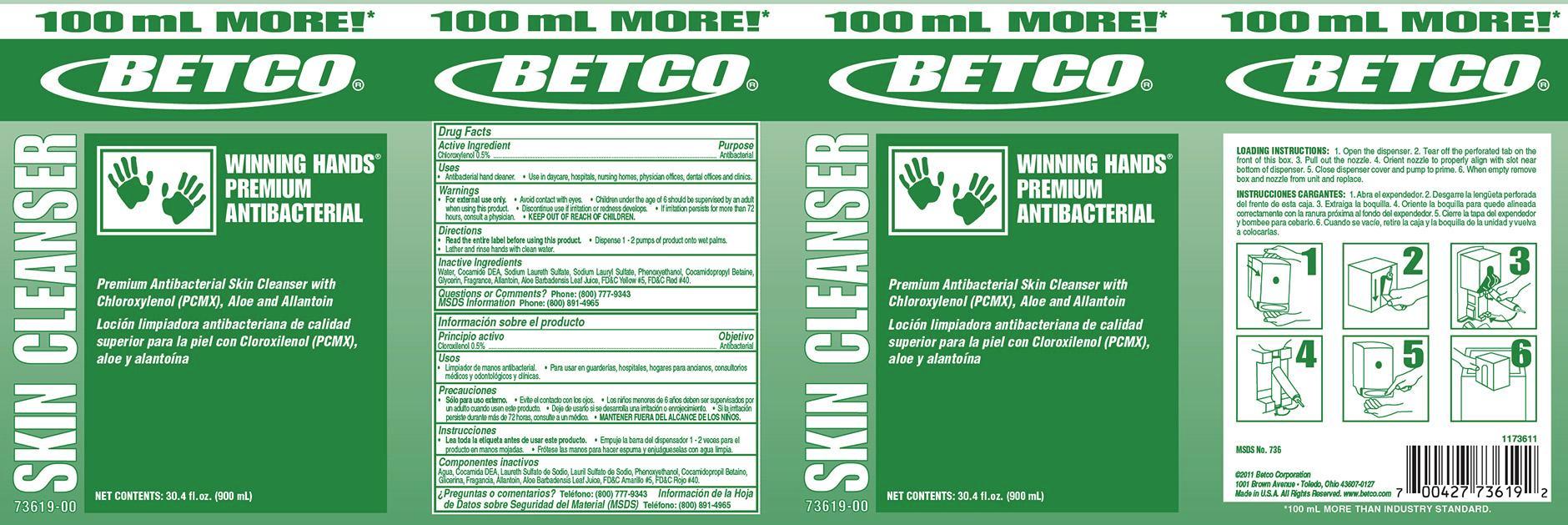 DRUG LABEL: Winning Hands Premium Antibacterial
NDC: 65601-736 | Form: SOAP
Manufacturer: Betco Corporation, Ltd.
Category: otc | Type: HUMAN OTC DRUG LABEL
Date: 20121112

ACTIVE INGREDIENTS: CHLOROXYLENOL 5.0 mg/1 mL
INACTIVE INGREDIENTS: WATER; SODIUM LAURYL SULFATE; COCO DIETHANOLAMIDE; COCAMIDOPROPYL BETAINE; PHENOXYETHANOL; SODIUM LAURETH SULFATE; ALLANTOIN; ALOE VERA LEAF; GLYCERIN; FD&C YELLOW NO. 5; FD&C RED NO. 40

Winning Hands Premium Antibacterial

Winning Hands Premium Antibacterial

Active Ingredient

Chloroxylenol 0.5%

Winning Hands Premium Antibacterial

Uses

- Antibacterial hand cleaner.
- Use in daycare, hospitals, nursing homes, physicians offices, dental offices and clinics

Winning Hands Premium Antibacterial

Warnings

- For external use only.
- Avoid contact with eyes.
- Children under the age of 6 should be supervised by an adult when using this product.
- Discontinue use is irritation or redness develops.
- If irritation persists for more than 72 hours, consult a physician.
- KEEP OUT OF REACH OF CHILDREN.

Winning Hands Premium Antibacterial

Directions

- Read the entire label before using this product.
- Dispense 1-2 pumps of product onto wet palm.
- Lather and rinse hands with clean water

Winning Hands Premium Antibacterial

Inactive Ingredients

Water, Sodium Lauryl lSulfate, Coco Diethanolimide, Cocamidopropyl Betaine, Phenoxyethanol, Sodium Laureth Sulfate, Allantoin, DMDM Hydantoin, Fragrance, Aloe Barbadensis Leaf Juice, Glycerine, FD&C Yellow #5, FD&C Red #40.

Winning Hands Premium Antibacterial

Questions or Comments? Phone: (800) 777-9343

MDS information:(800) 891-4965

Winning Hands Premium Antibacterial

Purpose

Antibacterial

Winning Hands Premium Antibacterial

KEEP OUT OF REACH OF CHILDREN

Winning Hands Premium Antibacterial

SKIN CLEANSER

Premium Antibacterial Skin Cleanser with Chloroxylenol (PCMX), Aloe and Allantoin

Net Contents: 30.4 fl. oz. (900 mL)